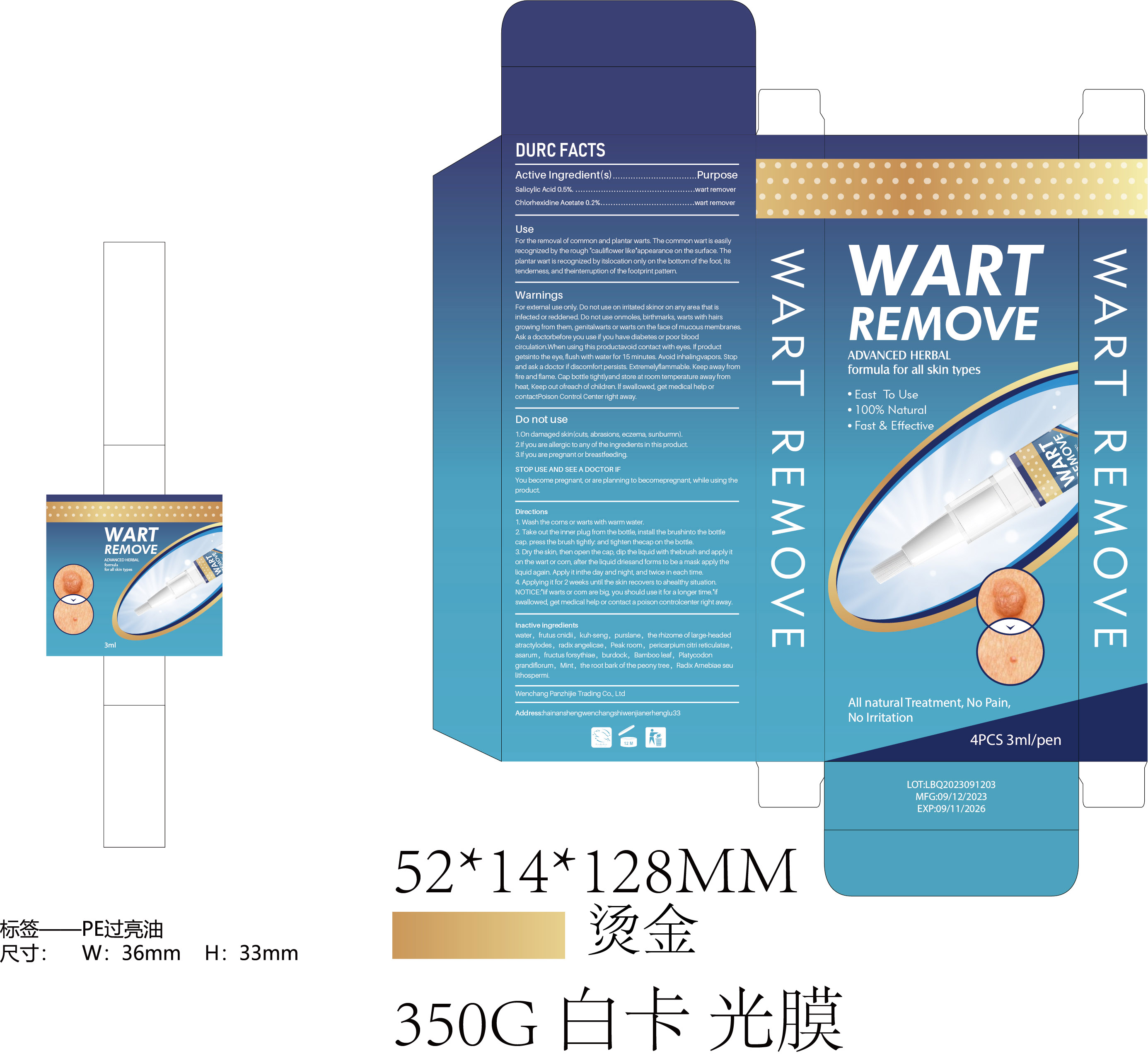 DRUG LABEL: wart removal pen
NDC: 83717-003 | Form: LIQUID
Manufacturer: Wenchang Panzhijie Trading Co., Ltd.
Category: otc | Type: HUMAN OTC DRUG LABEL
Date: 20231128

ACTIVE INGREDIENTS: CHLORHEXIDINE ACETATE 0.2 mg/100 mL; SALICYLIC ACID 0.5 mg/100 mL
INACTIVE INGREDIENTS: SOPHORA FLAVESCENS ROOT; ATRACTYLODES MACROCEPHALA WHOLE; FORSYTHIASIDE; PURSLANE; PLATYCODON GRANDIFLORUM ROOT; LITHOSPERMUM ERYTHRORHIZON ROOT; ASARUM VIRGINICUM WHOLE; ARCTIUM LAPPA WHOLE; CNIDIUM MONNIERI FRUIT; TANGERINE PEEL; PAEONIA SUFFRUTICOSA ROOT BARK; WATER; BAMBUSA VULGARIS LEAF; TRIPALMITOLEIN; ANGELICA DAHURICA WHOLE; MINT

83717-003

ACTIVE INGREDIENT

salicylic acid 0.5%

Chlorhexidine acetate 0.2%

Purpose

wart remover

Use

For the removal of common and plantar warts. The common wart is easily recognized by the rough " cauliflower like'appearance on the surface. The plantar wart is recognized by its location only on the bottom of the foot, itstenderness, and theinterruption of the footprint pattern.

Warnings

For external use only. Do not use on irritated skinor on any area that is infected or reddened. Do not use onmoles, birthmarks, warts with hairs growing from them, genitalwarts or warts on the face of mucous membranes. Ask a doctorbefore you use if you have diabetes or poor blood circulation When using this productavoid contact with eyes. If product getsinto the eye, flush with water for 15 minutes . Avoid inhalingvapors Stop and ask a doctor if discomfort persists. Extremelyflammable. Keep away from fire and flame. Cap bottle tightlyand store at room temperature away fror heat, Keep out ofreach of children. If swallowed, get medical help or contactpoison Control Center right away

Do not use

1 . On damaged skin (cuts , abrasions , eczema , sunburn)

2 . If you are allergic to any of the ingredients in this product .

3 . If you are pregnant or breastfeeding

STOP USE AND SEE A DOCTOR IF

You become pregnant , or are planning to becomepregnant , while using the product.

KEEP OUT OF REACH OF CHILDREN

Keep away freheat , Keep out ofreach of children . If swallowed , get medical help orcontactpoison Control Center right away.

Directions

1 . Wash the corns or warts with warm water

2 . Take out the inner plug from the bottle , install the brushinto the bottle cap. press the brush tightly and tighten theca on the bottle

3 . Dry the skin , then open the cap , dip the liquid with thebrush and apply it on the wart or com , after the liquid driesand forms to be a mask apply the liquid again . Apply it inthe day and night and twice in each time

4 . Applying it for 2 weeks until the skin recovers to ahealthy situation .

NOTICE : " lif warts or com are big , you should use it for a longer time . if swallowed , get medical help or contact a poison controlcenter right away

Inactive ingredients

water , frutus cnidii , kuh-seng , purslane , the rhizome of large-headed atractylodes , radix angelicae , Peak room , pericarpium citri reticulatae, asarum , fructus forsythiae , burdock , Bamboo leaf , Platycodon grandiflorum , Mint , the root bark of the peony tree , Radix Arnebiae seu lithosperm